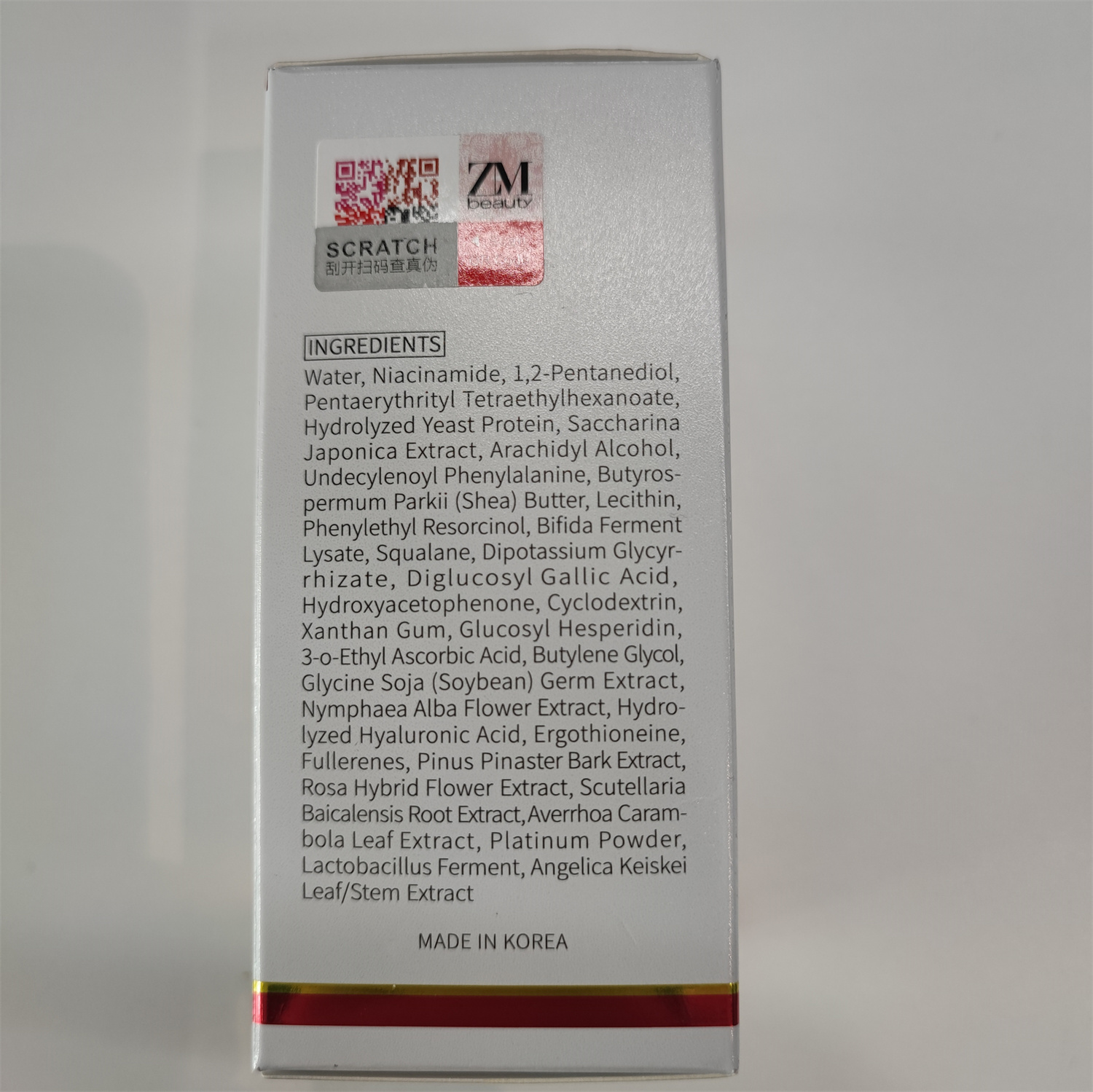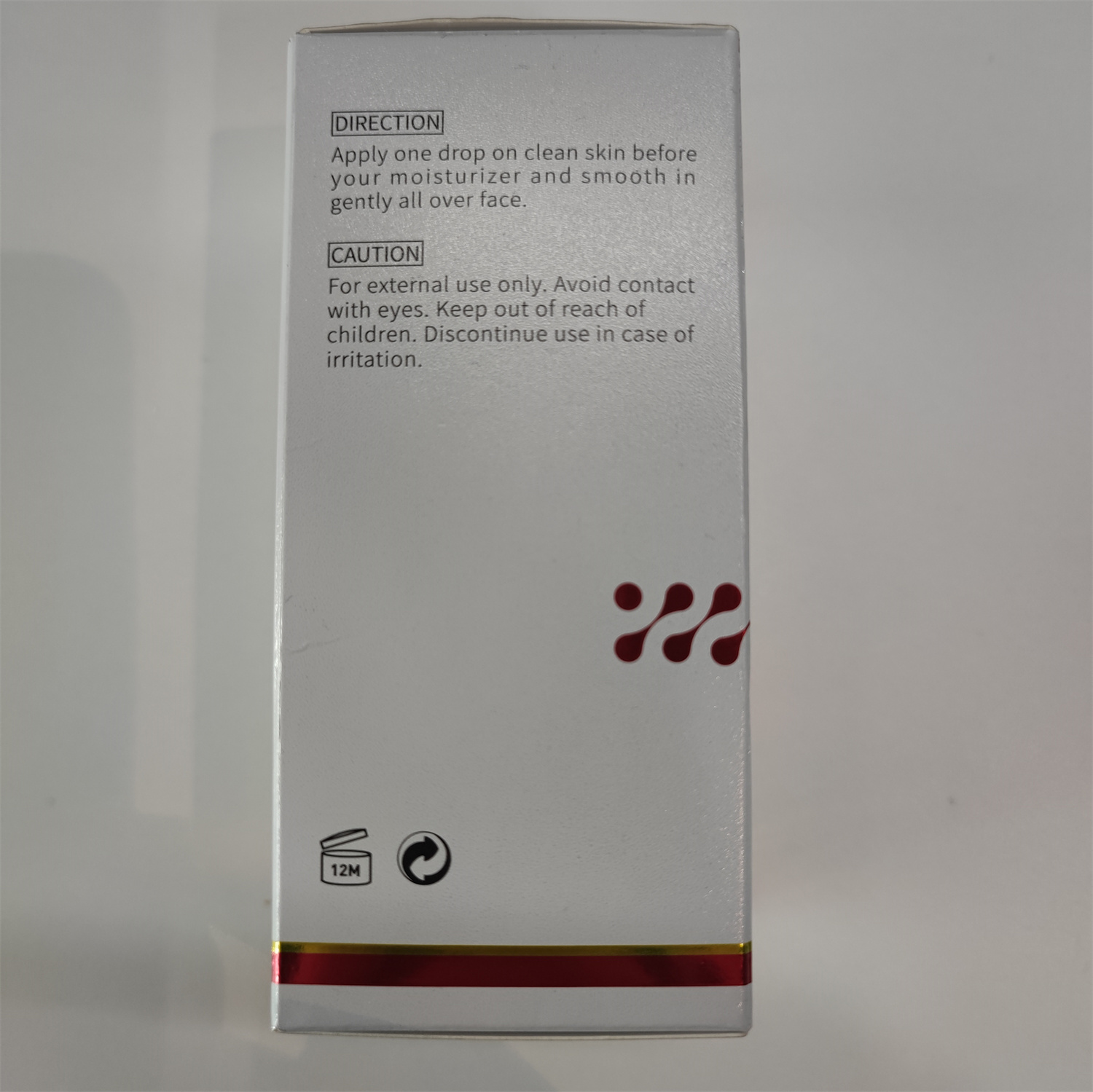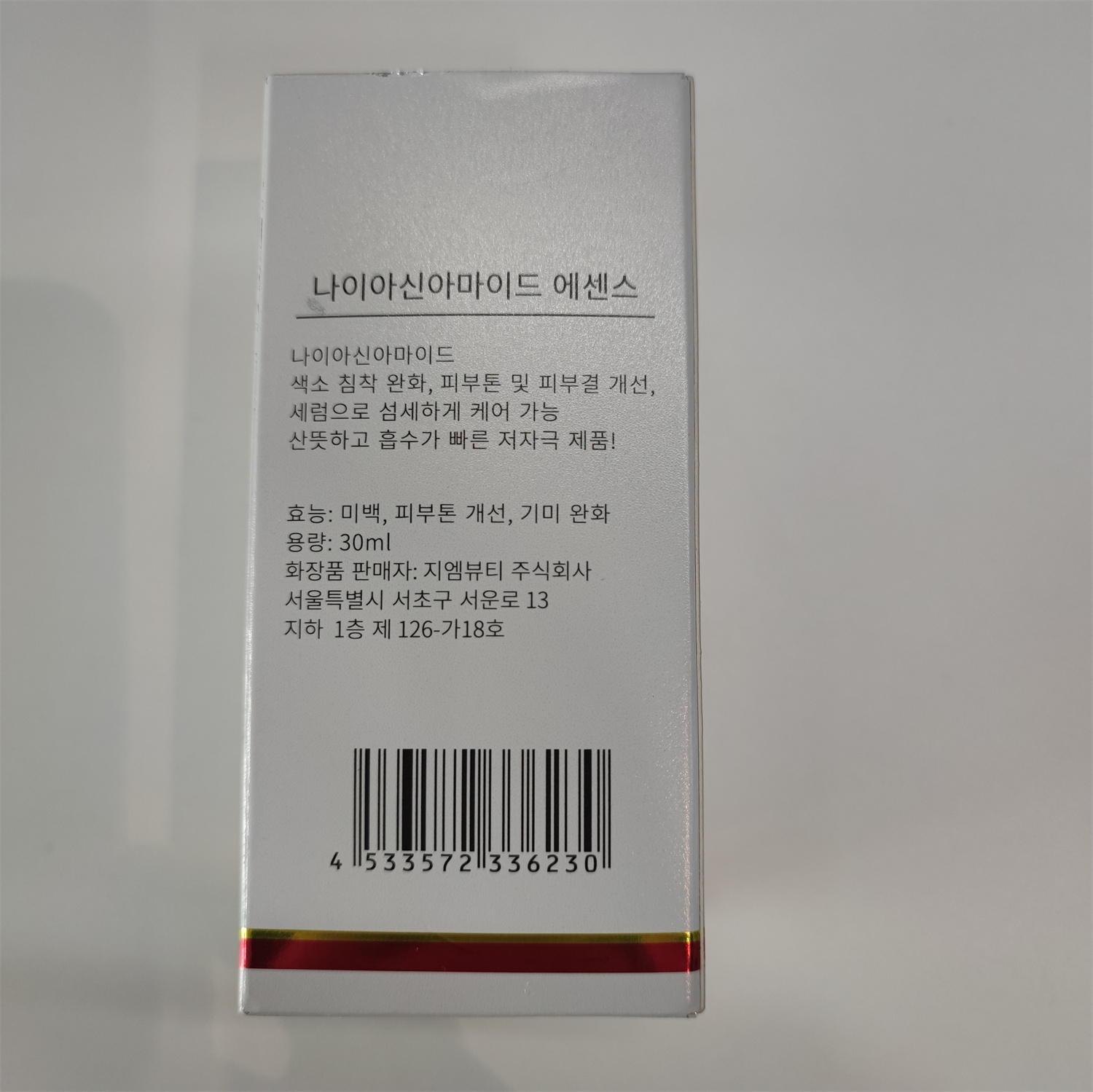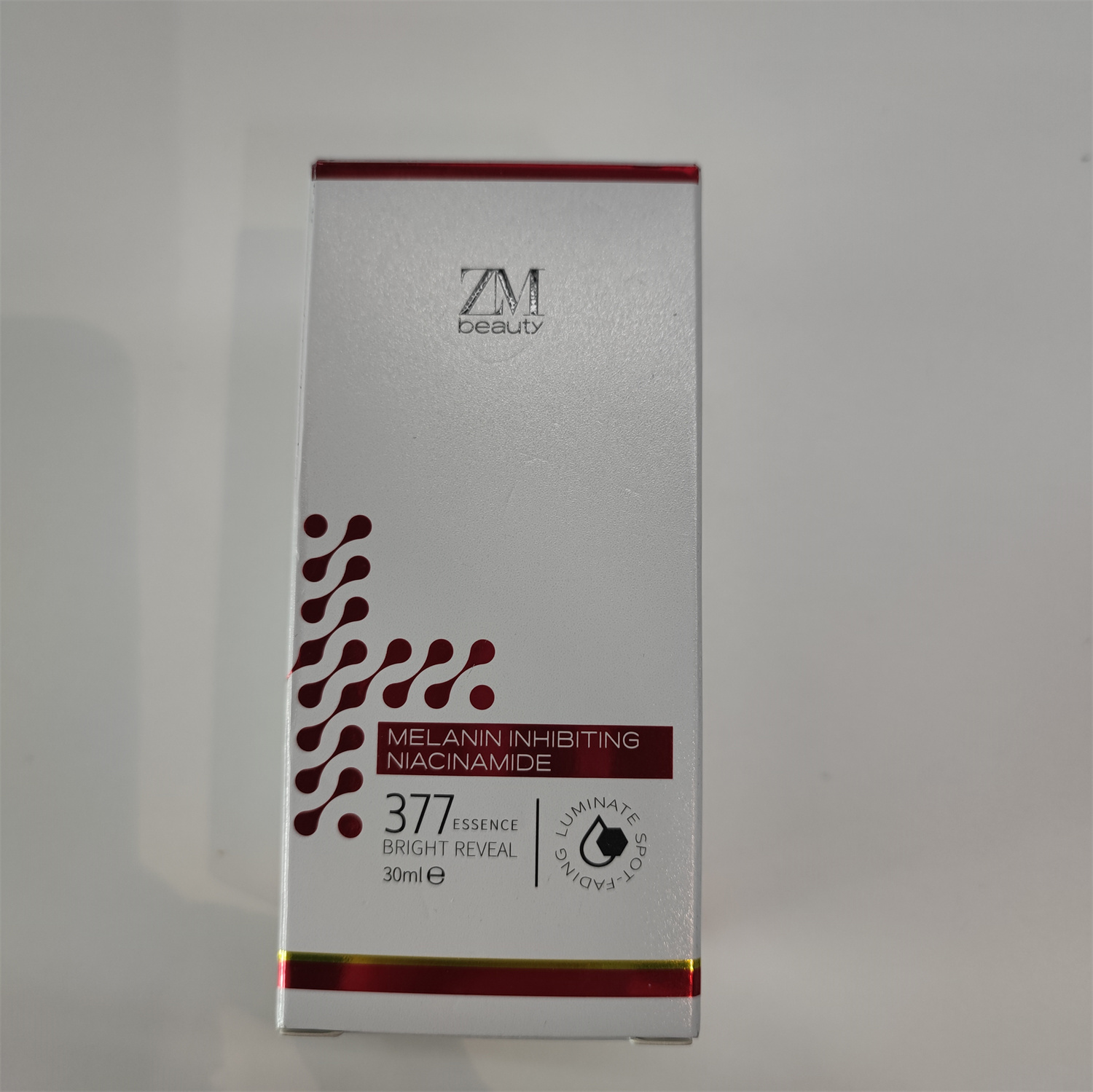 DRUG LABEL: 377 ESSENCE BRIGHT REVEAL
NDC: 84716-112 | Form: EMULSION
Manufacturer: Shenzhen Boyang E-commerce Co.
Category: otc | Type: HUMAN OTC DRUG LABEL
Date: 20241003

ACTIVE INGREDIENTS: NIACINAMIDE 1.5423 g/30 g; PENTYLENE GLYCOL 0.9 g/30 g; PENTAERYTHRITYL TETRAETHYLHEXANOATE 0.6 g/30 g
INACTIVE INGREDIENTS: WATER 26.154 g/30 g

ACTIVE INGREDIENTS

NIACINAMIDE 5.141%
PENTYLENE GLYCOL 3%
PENTAERYTHRITYL TETRAETHYLHEXANOATE 2%
HYDROLYZED YEAST PROTEIN 1%

PURPOSE

Can lighten hyperpigmentation, whiten, improve skin tone and texture, relieve wrinkles, meticulous care with lotion, refreshing, fast-absorbing, low irritation products.

uses

Apply one drop on clean skin before your moisturizer and smooth in gently all over face.

Warnings

For external use only.

Avoid contact with eyes.

Keep out of reach of children.

Discontinue use in case of irritation.

Stop use and ask a doctor if

lt is recommended to have a skin test (inside the wrist orbehind the ear) before use.If you feel uncomfortable,please stop using it.

Do not use

on damaged or broken skin

Keep out of reach of children.

Please place it out of the reach of infants；If swallowed, get medical help or contact a Poison Control Center right away.

When using this product

FOR EXTERNAL USE ONIY

keep out of eyes. Rinse with water to remove.

INACTIVE INGREDIENT SECTON

WATER，PLATINUM POWDER，XANTHAN GUM

uses and storage method

DIRECTION：
Apply one drop on clean skin before your moisturizer and smooth in gently all over face.
CAUTIONI：
For external use only.

Avoid contact with eyes.

Keep out of reach of children.

Discontinue use in case of irritation.

Please keep it in a cool and dry place and avoid light.